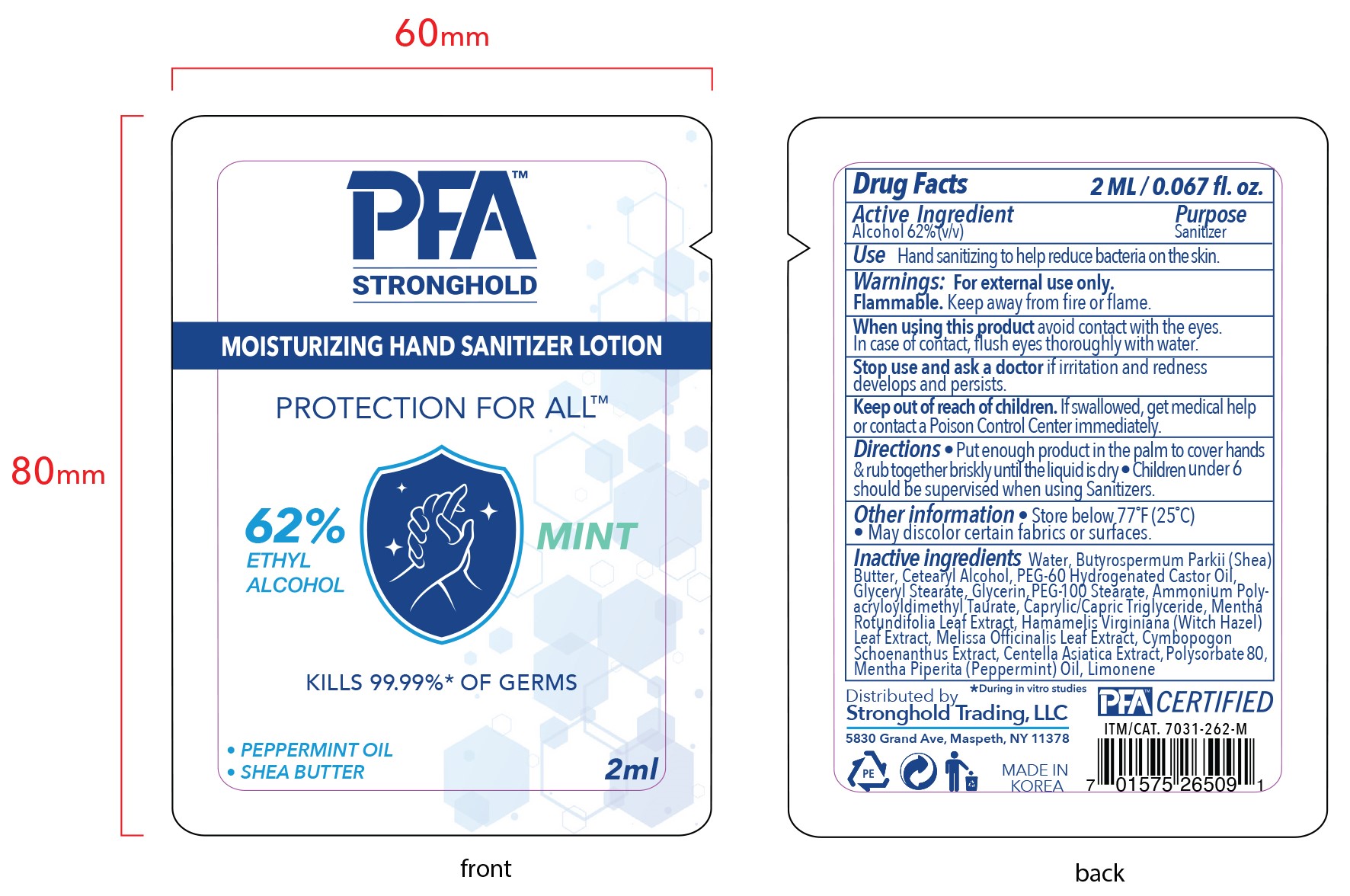 DRUG LABEL: PFA STRONGHOLD SANITIZING HANDLOTION MINT
NDC: 80969-006 | Form: LOTION
Manufacturer: STRONGHOLD TRADING LLC
Category: otc | Type: HUMAN OTC DRUG LABEL
Date: 20230125

ACTIVE INGREDIENTS: ALCOHOL 62 mL/100 mL
INACTIVE INGREDIENTS: MEDIUM-CHAIN TRIGLYCERIDES; WATER; CETOSTEARYL ALCOHOL; POLYOXYL 60 HYDROGENATED CASTOR OIL; MENTHA X ROTUNDIFOLIA LEAF; PEPPERMINT OIL; LIMONENE, (+)-; SHEA BUTTER; POLYSORBATE 80; HAMAMELIS VIRGINIANA LEAF; CYMBOPOGON SCHOENANTHUS TOP; GLYCERYL MONOSTEARATE; GLYCERIN; POLYOXYL 100 STEARATE; AMMONIUM POLYACRYLOYLDIMETHYL TAURATE (55000 MPA.S); MELISSA OFFICINALIS LEAF; CENTELLA ASIATICA TRITERPENOIDS

80969-006-01 PFA STRONGHOLD SANITIZING HAND LOTION_MINT

Active ingredient

Alcohol 62%

Purpose

Sanitizer

Use

Hand sanitizing to help reduce bacteria on the skin.

Warnings

For external use only.

Flammable. Keep away from fire or flame.

When using this product

avoid contact with the eyes.

In case of contact, flush eyes thoroughly with water.

Stop use and ask a doctor

if irritation and redness develops and persists.

Keep out of reach of children.

If swallowed, get medical help or contact a Poison Control Center immediately.

Directions

- Put enough product in the palm to cover hands & rub together briskly the liquid is dry
- Children under 6 should be supervised when using Sanitizers.

Other information

- Store below 77°F (25°C)
- May discolor certain fabrics or surfaces.

Inactive ingredients

Water, Butyrospermum Parkii (Shea) Butter, Cetearyl Alcohol, PEG-60 Hydrogenated Castor Oil, Glyceryl Stearate, Glycerin, PEG-100 Stearate, Ammonium Polyacryloyldimethyl Taurate, Caprylic/Capric Triglyceride, Mentha Rotundifolia Leaf Extract, Hamamelis Virginiana (Witch Hazel) Leaf Extract, Melissa Officinalis Leaf Extract, Cymbopogon Schoenanthus Extract, Centella Asiatica Extract, Polysorbate 80, Mentha Piperita (Peppermint) Oil, Limonene